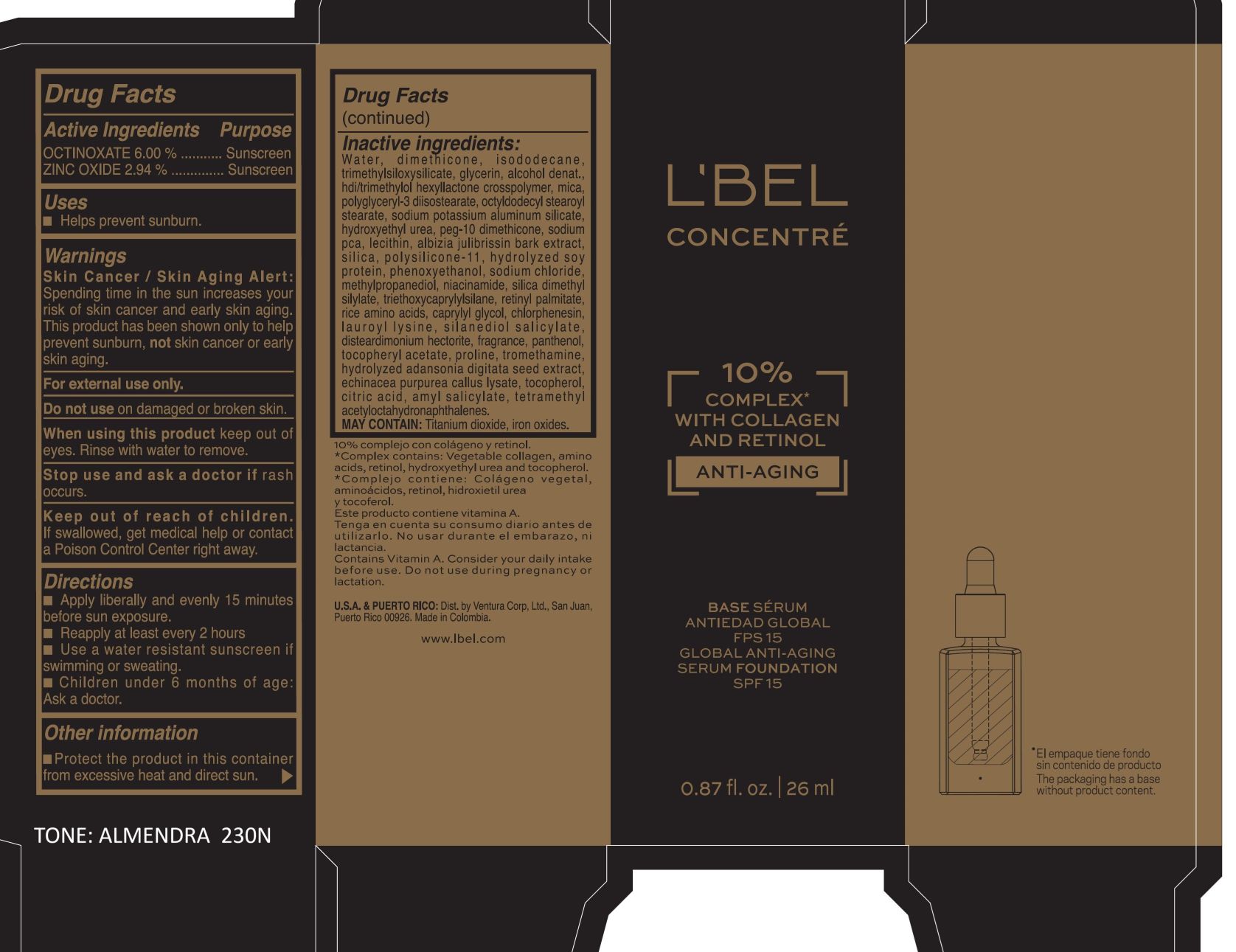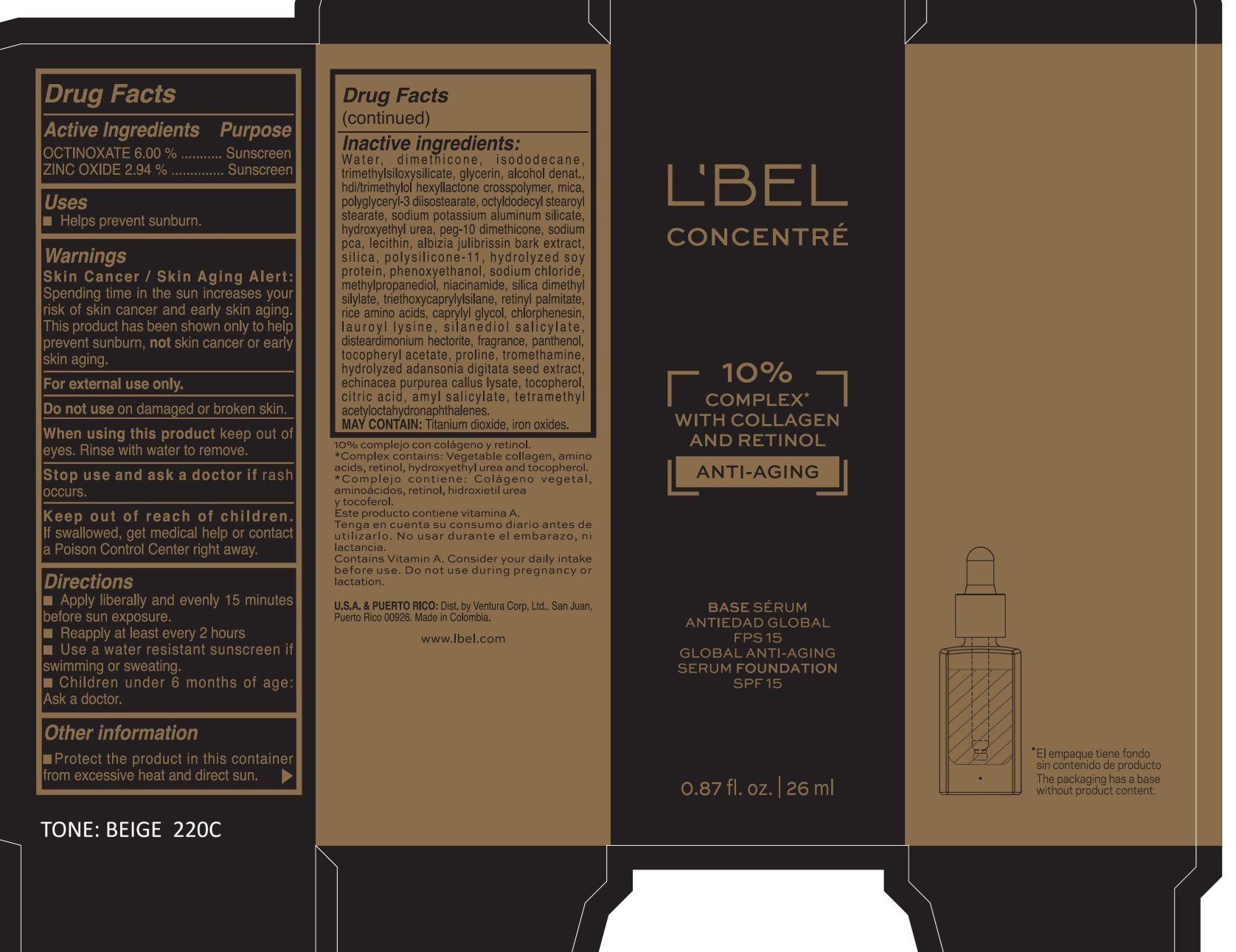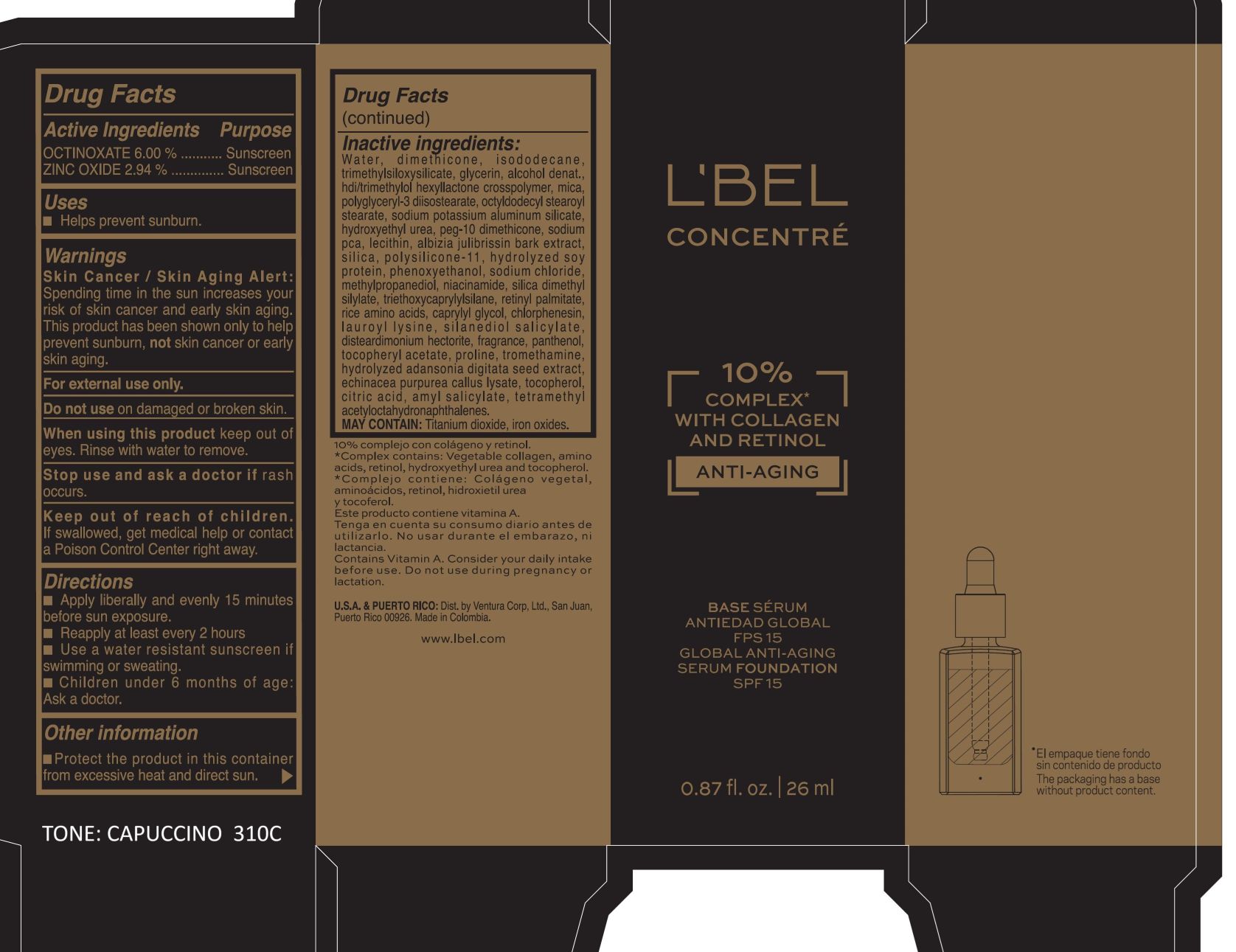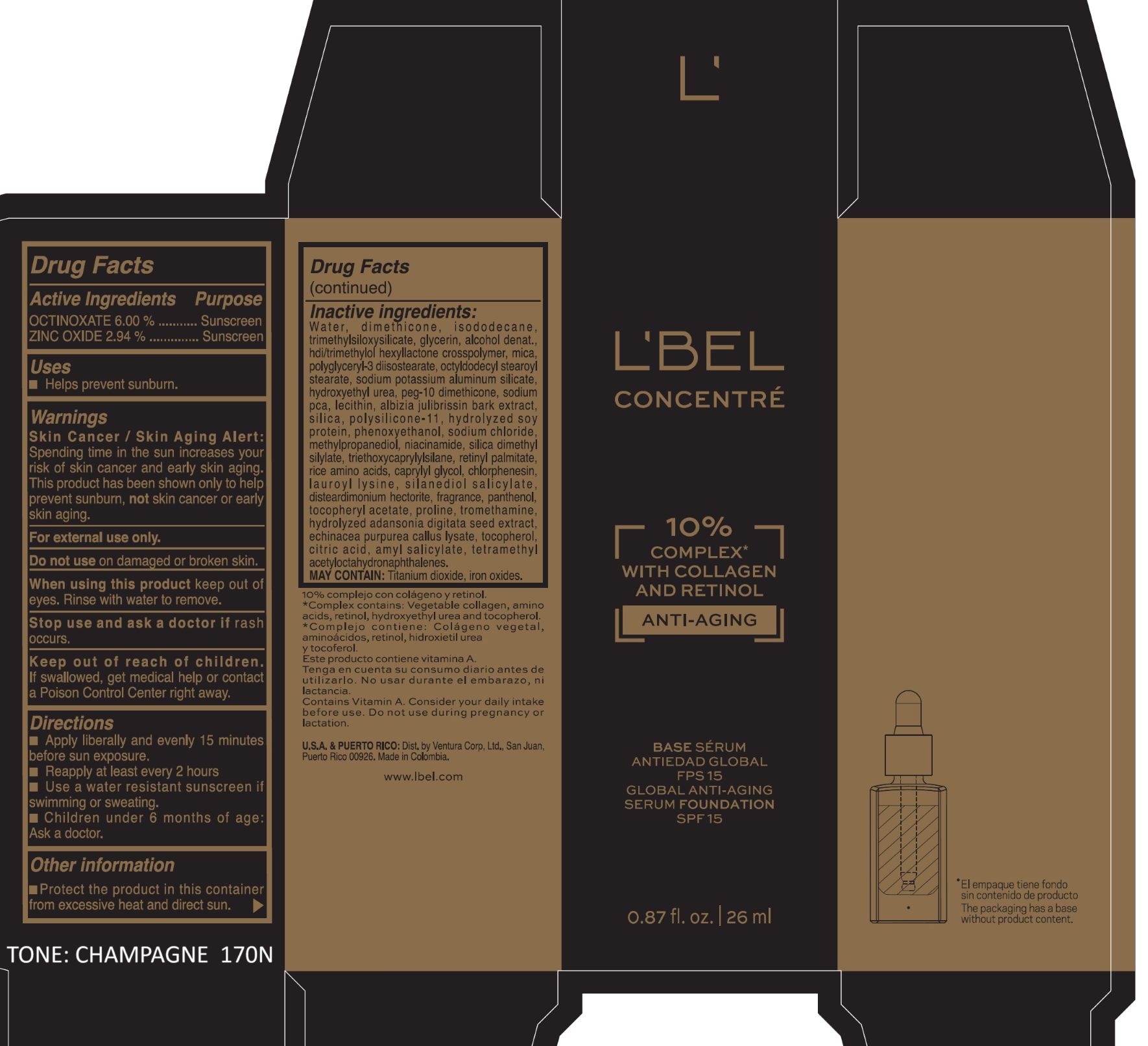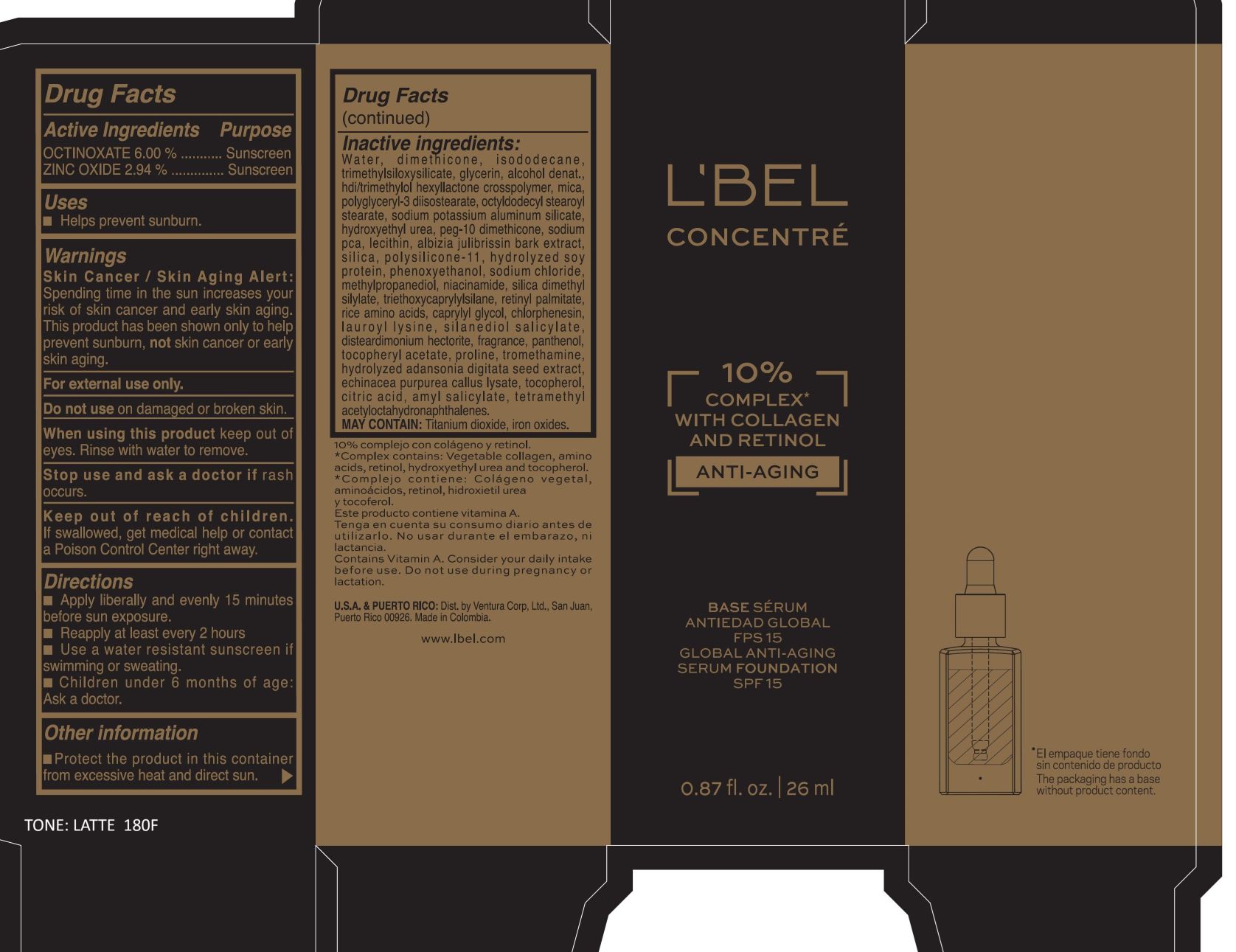 DRUG LABEL: LBEL CONCENTRE GLOBAL ANTI AGING SERUM FOUNDATION SPF 15 LATTE 180F
NDC: 14141-375 | Form: EMULSION
Manufacturer: BEL STAR S.A.
Category: otc | Type: HUMAN OTC DRUG LABEL
Date: 20250821

ACTIVE INGREDIENTS: OCTINOXATE 60 mg/1 mL; ZINC OXIDE 29.4 mg/1 mL
INACTIVE INGREDIENTS: GLYCERIN; POLYGLYCERYL-3 DIISOSTEARATE; NIACINAMIDE; SODIUM POTASSIUM ALUMINUM SILICATE; SILICA DIMETHYL SILYLATE; CITRIC ACID MONOHYDRATE; SODIUM CHLORIDE; ALPHA-TOCOPHEROL ACETATE; PANTHENOL; PROLINE; AMYL SALICYLATE; HDI/TRIMETHYLOL HEXYLLACTONE CROSSPOLYMER; DISTEARDIMONIUM HECTORITE; TETRAMETHYL ACETYLOCTAHYDRONAPHTHALENES; MICA; TRIETHOXYCAPRYLYLSILANE; PEG-10 DIMETHICONE (600 CST); SODIUM PCA; LECITHIN, SUNFLOWER; SILANEDIOL SALICYLATE; WATER; HYDROLYZED SOY PROTEIN (ENZYMATIC; 2000 MW); METHYLPROPANEDIOL; RETINYL PALMITATE; TROMETHAMINE; SILICON DIOXIDE; DIMETHICONE/VINYL DIMETHICONE CROSSPOLYMER (SOFT PARTICLE); ISODODECANE; PHENOXYETHANOL; TITANIUM DIOXIDE; CAPRYLYL GLYCOL; RICE AMINO ACIDS; TOCOPHEROL; FERROUS OXIDE; CHLORPHENESIN; DIMETHICONE; HYDROXYETHYL UREA; TRIMETHYLSILOXYSILICATE (M/Q 0.66); LAUROYL LYSINE; OCTYLDODECYL STEAROYL STEARATE; ALCOHOL; ALBIZIA JULIBRISSIN BARK

LBEL CONCENTRE GLOBAL ANTI AGING SERUM FOUNDATION SPF 15

Active Ingredients

OCTINOXATE 6.00%

ZINC OXIDE 2.94%

Purpose

Sunscreen

Uses

- Helps prevent sunburn.

Warnings

Skin Cancer / Skin Aging Alert: Spending time in the sun increases your risk of skin cancer and early skin aging. This product has been shown only to help prevent sunburn, not skin cancer or early skin aging.

For external use only.

Do not use

on damaged or broken skin.

When using this product

keep out of eyes. Rinse with water to remove.

Stop use and ask a doctor if

rash occurs.

Keep out of reach of children.

If swallowed, get medical help or contact a Poison Control Center right away.

Directions

- Apply liberally and evenly 15 minutes before sun exposure.
- Reapply at least every 2 hours
- Use a water resistant sunscreen if swimming or sweating.
- Children under 6 months of age: Ask a doctor

Other information

- Protect the product in this container from excessive heat and direct sun.

Inactive ingredients

Water, dimethicone, isododecane, trimethylsiloxysilicate, glycerin, alcohol denat., hdi/trimethylol hexyllactone crosspolymer, mica, polyglyceryl-3 diisostearate, octyldodecyl stearoyl stearate, sodium potassium aluminum silicate, hydroxyethyl urea, peg-10 dimethicone, sodium pca, lecithin, albizia julibrissin bark extract, silica, polysilicone-11, hydrolyzed soy protein, phenoxyethanol, sodium chloride, methylpropanediol, niacinamide, silica dimethyl silylate, triethoxycaprylylsilane, retinyl palmitate, rice amino acids, caprylyl glycol, chlorphenesin, lauroyl lysine, silanediol salicylate, disteardimonium hectorite, fragrance, panthenol, tocopheryl acetate, proline, tromethamine, hydrolyzed adansonia digitata seed extract, echinacea purpurea callus lysate, tocopherol, citric acid, amyl salicylate, tetramethyl acetyloctahydronaphthalenes.

MAY CONTAIN : Titanium dioxide, iron oxides.